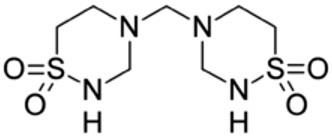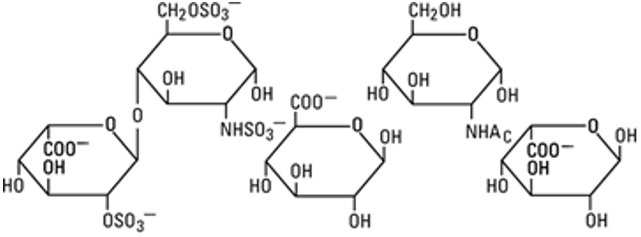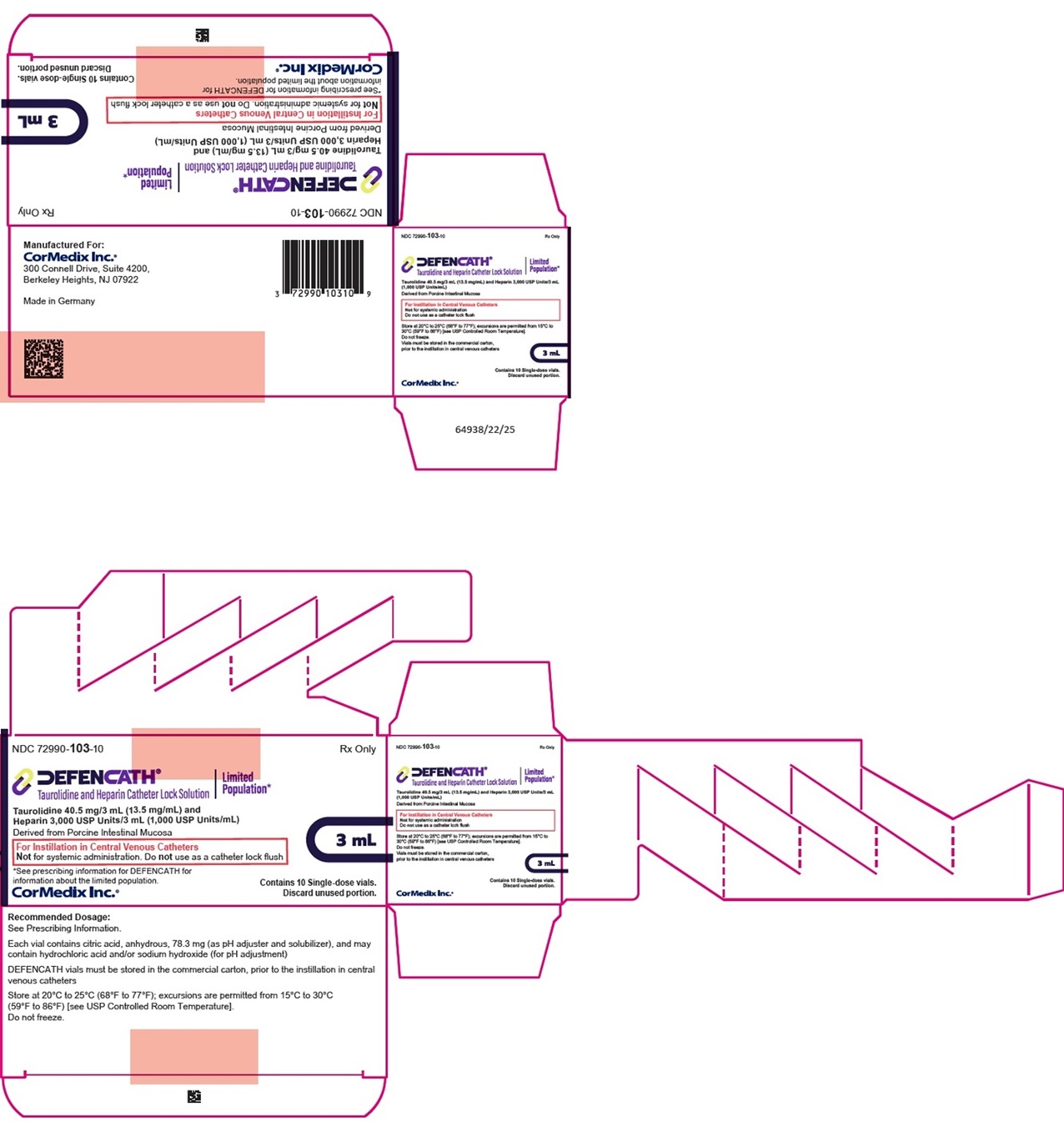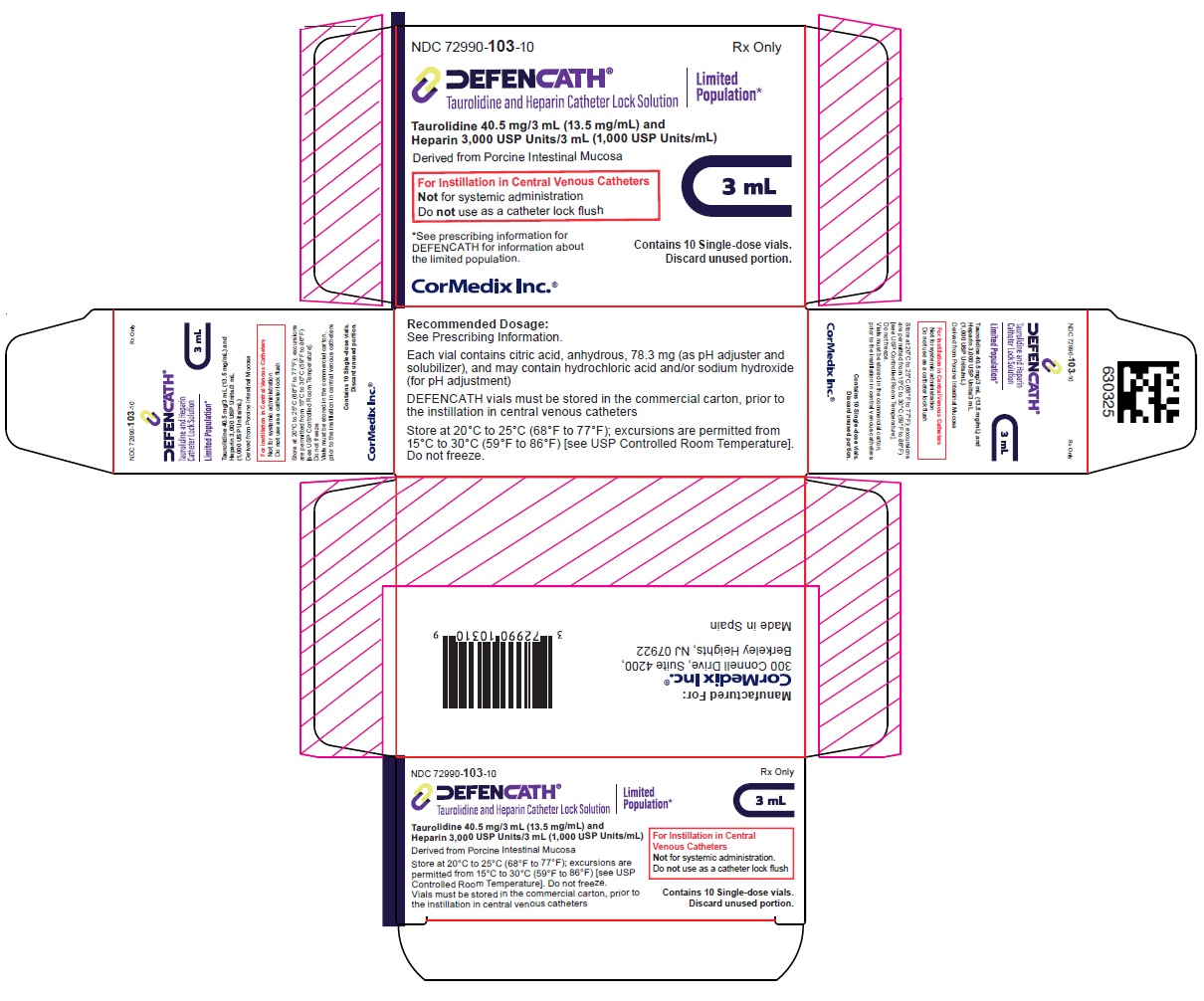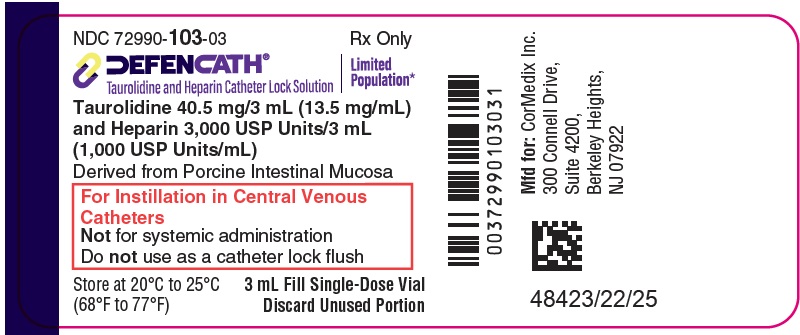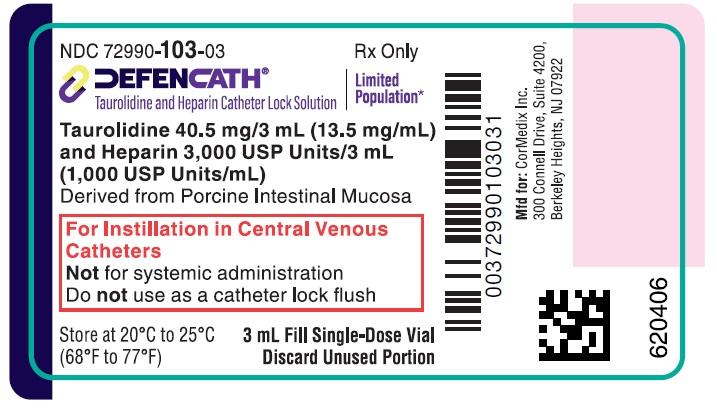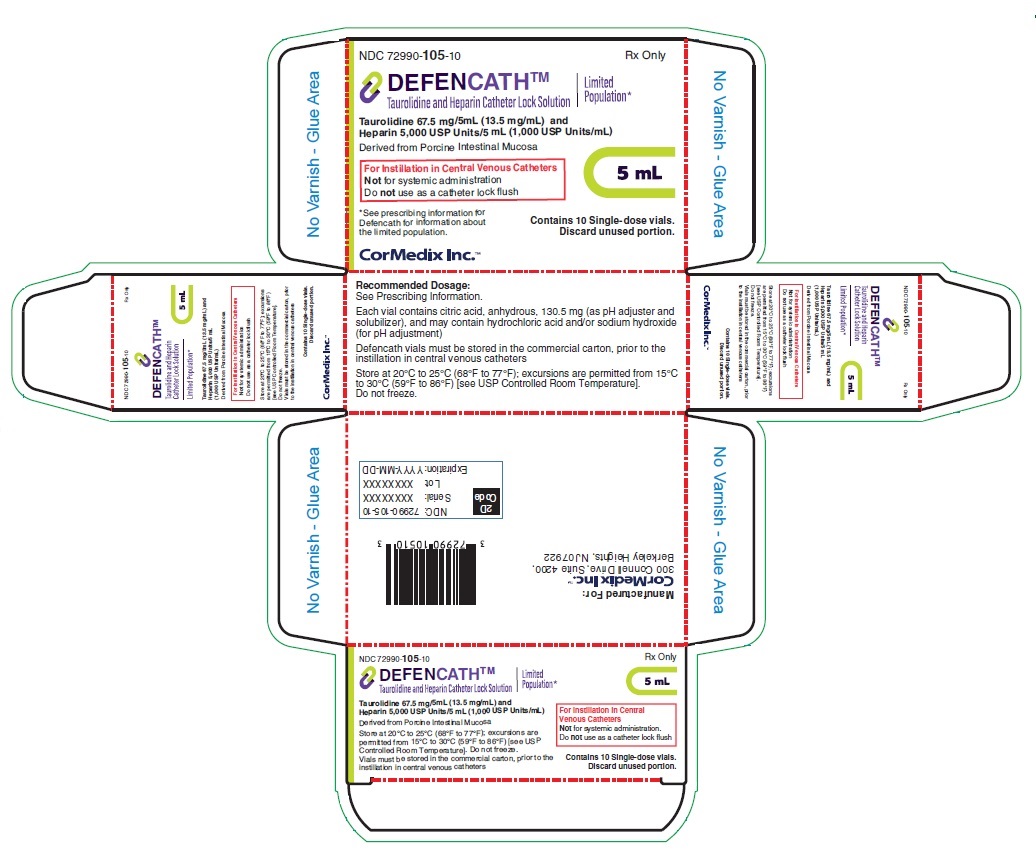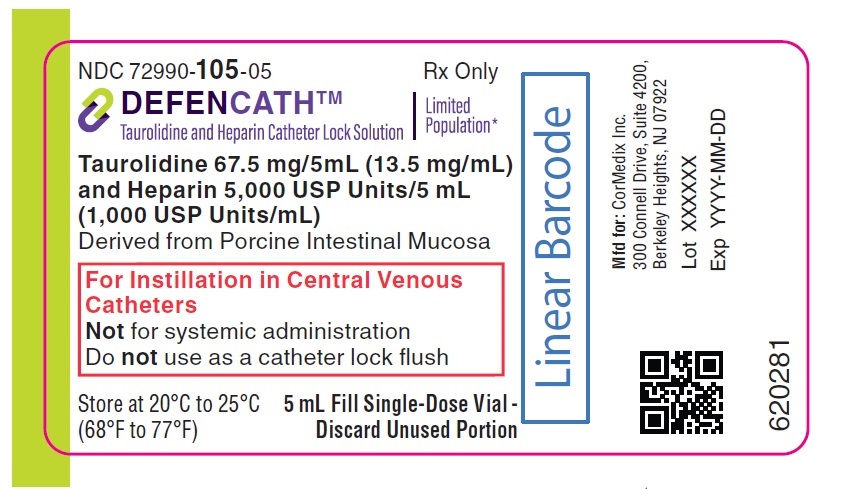 DRUG LABEL: DEFENCATH
NDC: 72990-103 | Form: SOLUTION
Manufacturer: CorMedix Inc.
Category: prescription | Type: HUMAN PRESCRIPTION DRUG LABEL
Date: 20250929

ACTIVE INGREDIENTS: TAUROLIDINE 40.5 mg/3 mL; HEPARIN 3000 [USP'U]/3 mL
INACTIVE INGREDIENTS: ANHYDROUS CITRIC ACID 78.3 mg/3 mL; HYDROCHLORIC ACID; SODIUM HYDROXIDE

HIGHLIGHTS OF PRESCRIBING INFORMATION

These highlights do not include all the information needed to use DEFENCATH safely and effectively. See full prescribing information for DEFENCATH.
DEFENCATH® (taurolidine and heparin) catheter lock solution, for central venous catheter instillation use
Initial U.S. Approval: 2023
LIMITED POPULATION

RECENT MAJOR CHANGES

Dosage and Administration (2) | 12/2024

1 INDICATIONS AND USAGE

LIMITED POPULATION: DEFENCATH is a combination of taurolidine, a thiadiazinane antimicrobial, and heparin, an anti-coagulant, indicated to reduce the incidence of catheter-related bloodstream infections (CRBSI) in adult patients with kidney failure receiving chronic hemodialysis (HD) through a central venous catheter (CVC). This drug is indicated for use in a limited and specific population of patients. (1)

Limitations of Use

The safety and effectiveness of DEFENCATH have not been established for use in populations other than adult patients with kidney failure receiving chronic HD through a CVC. (1)

2 DOSAGE AND ADMINISTRATION

- DEFENCATH is for instillation into CVCs only. (2)
- DEFENCATH is not intended for systemic administration. (2)
- Do not use DEFENCATH as a catheter lock flush product. (2)
- Withdraw a sufficient volume of DEFENCATH catheter lock solution (CLS) from the vial using a sterile needle and syringe to fill the catheter lumens. (2)
- Use 3 mL or 5 mL single dose vial (depending on the volume of the catheter lumens) to instill DEFENCATH into each catheter lumen at the conclusion of each HD session. (2)
- DEFENCATH should be aspirated from the catheter and discarded prior to the initiation of the next HD session. (2)
- Discard any unused portion of DEFENCATH remaining in the vial. (2)

3 DOSAGE FORMS AND STRENGTHS

- DEFENCATH is a sterile catheter lock solution available in single-dose vials in the following strengths:
  - 3 mL containing taurolidine 40.5 mg/3 mL (13.5 mg/mL), and heparin 3,000 USP Units/3 mL (1,000 USP Units/mL) (3)
  - 5 mL containing taurolidine 67.5 mg/5 mL (13.5 mg/mL), and heparin 5,000 USP Units/5 mL (1,000 USP Units/mL) (3)

4 CONTRAINDICATIONS

- Known heparin-induced thrombocytopenia. (4)
- Known hypersensitivity to taurolidine, heparin or the citrate excipient (components of DEFENCATH), or pork products. (4)

5 WARNINGS AND PRECAUTIONS

- Heparin-Induced Thrombocytopenia (HIT): HIT was reported in Trial 1 at an incidence rate of 0.3% in patients using heparin, a component of DEFENCATH as a CLS. If HIT occurs, discontinue DEFENCATH and institute appropriate supportive measures. (5.1)
- Drug Hypersensitivity Reactions: Drug hypersensitivity reactions were reported in Trial 1 at an incidence rate of 0.5% in patients using heparin, a component of DEFENCATH, as a CLS. If a hypersensitivity reaction occurs, discontinue DEFENCATH and institute appropriate supportive measures. (5.2)

6 ADVERSE REACTIONS

The most frequently reported adverse reactions occurring in greater than or equal to 2% of patients in Trial 1 using DEFENCATH as a CLS were hemodialysis catheter malfunction, hemorrhage/bleeding, nausea, vomiting, dizziness, musculoskeletal chest pain, and thrombocytopenia. (6.1)

To report SUSPECTED ADVERSE REACTIONS, contact CorMedix Inc at 1-844-424-6345 or FDA at 1-800-FDA-1088 or www.fda.gov/medwatch.

FULL PRESCRIBING INFORMATION

1 INDICATIONS AND USAGE

LIMITED POPULATION: DEFENCATH® is indicated to reduce the incidence of catheter-related bloodstream infections (CRBSI) in adult patients with kidney failure receiving chronic hemodialysis (HD) through a central venous catheter (CVC). This drug is indicated for use in a limited and specific population of patients [see Clinical Studies (14)].

Limitations of Use

The safety and effectiveness of DEFENCATH have not been established for use in populations other than adult patients with kidney failure receiving chronic HD through a CVC.

2 DOSAGE AND ADMINISTRATION

DEFENCATH is for instillation into CVCs only [see Indications and Usage (1)]. DEFENCATH is not intended for systemic administration. Do not use DEFENCATH as a catheter lock flush product.

Withdraw a sufficient volume of DEFENCATH catheter lock solution (CLS) from the vial using a sterile needle and syringe to fill the catheter lumens. Use 3 mL or 5 mL single-dose vial (depending on the volume of the catheter lumens) to instill DEFENCATH into each catheter lumen at the conclusion of each HD session for patients with kidney failure requiring chronic HD. Prior to initiation of the next HD session, DEFENCATH should be aspirated from the catheter and discarded. If DEFENCATH cannot be aspirated, continue with standard of care CVC preparation and flush with normal saline. If a catheter malfunction is suspected, appropriate standard of care measures should be instituted.

Each DEFENCATH single-dose vial is designed for use with a single patient as a single instillation in the CVC. Discard any unused portion of DEFENCATH remaining in the vial.

3 DOSAGE FORMS AND STRENGTHS

DEFENCATH CLS is available as a sterile, preservative-free, clear, aqueous-based solution in the following strengths:

- 3 mL of catheter lock solution in a single-dose vial containing taurolidine 40.5 mg/3 mL (13.5 mg/mL), and heparin 3,000 USP Units/3 mL (1,000 USP Units/mL)
- 5 mL of catheter lock solution in a single-dose vial containing taurolidine 67.5 mg/5 mL (13.5 mg/mL), and heparin 5,000 USP Units/5 mL (1,000 USP Units/mL)

4 CONTRAINDICATIONS

DEFENCATH is contraindicated in patients with:

- Known heparin-induced thrombocytopenia (HIT) [see Warnings and Precautions (5.1)].
- Known hypersensitivity to taurolidine, heparin or the citrate excipient (components of DEFENCATH) or pork products [see Warnings and Precautions (5.2)].

5 WARNINGS AND PRECAUTIONS

5.1 Heparin-Induced Thrombocytopenia

Heparin-induced thrombocytopenia (HIT) was reported at an incidence rate of 0.3% in Trial 1 in patients using heparin, a component of DEFENCATH, as a CLS. If HIT occurs, discontinue DEFENCATH and institute appropriate supportive measures [see Contraindications (4)].

5.2 Drug Hypersensitivity

Drug hypersensitivity reactions were reported at an incidence rate of 0.5% in Trial 1 in patients using heparin, a component of DEFENCATH, as a CLS. If a hypersensitivity reaction occurs, discontinue DEFENCATH and institute appropriate supportive measures [see Contraindications (4)].

6 ADVERSE REACTIONS

The following clinically significant adverse reactions are described elsewhere in the labeling:

- Heparin-Induced Thrombocytopenia [see Warnings and Precautions (5.1)]
- Drug Hypersensitivity [see Warnings and Precautions (5.2)]

6.1 Clinical Trials Experience

Because clinical trials are conducted under widely varying conditions, adverse reaction rates observed in the clinical trials of a drug cannot be directly compared to rates in the clinical trials of another drug and may not reflect the rates observed in practice.

Overview of the Safety Evaluation of DEFENCATH

The safety of DEFENCATH was evaluated in a single, active-controlled, double-blind, randomized Phase 3 trial, LOCK-IT-100 (referred to as Trial 1), in adult patients with kidney failure receiving chronic HD through a CVC. In Trial 1, the safety population was comprised of 797 patients with 398 patients using DEFENCATH as a CLS and 399 using heparin as a CLS. Patients used DEFENCATH as a CLS for a mean duration of 173 days, and a range of 4 to 863 days.

The mean age of the patients in Trial 1 was 61 years, 58% of patients identified as male (42% patients identified as female), 63% of patients identified as white and 30% identified as black or African-American. Patients with diabetes at baseline accounted for 70% of patients and the mean body mass index (BMI) of patients in the study was 30. The majority of patients (68%) had been receiving HD for 12 months or less. The location of the CVC was the jugular vein in 92% of patients.

Serious Adverse Reactions and Adverse Reactions Leading to Discontinuation

In Trial 1, serious adverse reactions occurred in 40% (159/398) of patients receiving DEFENCATH as a CLS and 42% (167/399) of patients receiving heparin as a CLS. Adverse reactions leading to death occurred in 5% (18/398) of patients in the DEFENCATH arm and 5% (21/399) of patients in the heparin arm.

Adverse reactions leading to discontinuation of study drug occurred in 17% (69/398) of patients in the DEFENCATH arm and 18% (72/399) of patients in the heparin arm.

Common Adverse Reactions

In Trial 1, adverse reactions were reported in 79% (314/398) of patients using DEFENCATH as a CLS and 79% (315/399) of patients using heparin.

Table 1 lists selected adverse reactions occurring in ≥2% of patients using DEFENCATH or heparin in Trial 1.

Table 1: Selected Adverse Reactions Occurring in Greater Than or Equal to 2% of Patients Receiving DEFENCATH in Trial 1
Adverse Reactions | DEFENCATH (N=398) N (%) | Heparin (N=399) N (%)
Product Issues
Hemodialysis catheter malfunction [Grouped term includes device malfunction] | 68 (17) | 47 (12)
Blood and lymphatic system disorders
Hemorrhage/bleeding [Grouped term includes: hematoma/hemorrhage, intracranial hemorrhage, arteriovenous graft or fistula site hemorrhage, catheter site hematoma/hemorrhage, cerebral/cerebellar hemorrhage, eye/conjunctival hemorrhage, gastrointestinal hemorrhage, hematuria, hemobilia, hemoptysis, renal hematoma, vaginal/uterine hemorrhage] | 27 (7) | 34 (9)
Thrombocytopenia | 7 (2) | 4 (1)
Gastrointestinal disorders
Nausea [Grouped term includes nausea and procedural nausea] | 28 (7) | 44 (11)
Vomiting [Grouped term includes vomiting and procedural vomiting] | 24 (6) | 32 (8)
Nervous system disorders
Dizziness | 22 (6) | 16 (4)
Musculoskeletal and Connective Tissue Disorders
Musculoskeletal chest pain [Grouped term Includes non-cardiac chest pain, musculoskeletal chest pain, chest discomfort] | 11 (3) | 7 (2)

Table 2 lists the proportion of patients in Trial 1 that developed loss of catheter patency defined as requiring use of a thrombolytic agent to resolve catheter thrombosis or removal of the catheter due to malfunction/dysfunction.

Table 2: Loss of Catheter Patency in Trial 1
 | DEFENCATH (N=398) N (%) | Heparin (N=399) N (%)
Loss of Catheter Patency | 63 (16) | 48 (12)
Use of a Thrombolytic Agent [11 subjects in each arm had catheter removal following thrombolytic agent use and are included under both categories of use of a thrombolytic agent and catheter removal.] | 46 (12) | 33 (8)
Catheter Removal [Catheter removal refers to catheters removed due to loss of catheter patency. Overall, a total of 236 patients in the DEFENCATH arm and 225 patients in the heparin arm had a catheter removal for any reason, including loss of catheter patency.] | 28 (7) | 26 (7)
Catheter Removal without Thrombolytic Agent Use | 17 (4) | 15 (4)

Other Adverse Reactions

Clinically significant adverse reactions that occurred in fewer than 1% of patients receiving DEFENCATH in Trial 1 are listed below:

Metabolism and Nutrition Disorders: Hypocalcemia

Nervous System Disorders: Dysgeusia

6.2 Postmarketing Experience

The following adverse reaction has been identified during the use of a taurolidine and heparin containing CLS outside of the United States. Because this reaction is reported from a population of uncertain size, it is not always possible to reliably estimate its frequency or establish a causal relationship to drug exposure.

Nervous System Disorders: Paresthesia

8 USE IN SPECIFIC POPULATIONS

8.1 Pregnancy

Risk Summary

DEFENCATH is not intended for systemic administration. It is intended for use as a CLS in patients with kidney failure requiring chronic HD; therefore, maternal use is not expected to result in fetal exposure to the drug [see Dosage and Administration (2)]. No animal reproduction study was conducted with DEFENCATH.

8.2 Lactation

Risk Summary

DEFENCATH is not intended for systemic administration. It is intended for use as a CLS in patients with kidney failure requiring chronic HD; therefore, breastfeeding is not expected to result in exposure of the infant to DEFENCATH [see Dosage and Administration (2)].

8.4 Pediatric Use

The safety and effectiveness of DEFENCATH have not been established in pediatric patients. There are no available data on DEFENCATH use in pediatric patients.

8.5 Geriatric Use

There were 327 patients 65 years of age and older in Trial 1 [see Clinical Studies (14)]. Of the total number of patients using DEFENCATH in this study, 162 (41%) were 65 years of age and older, while 64 (16%) were 75 years of age and older. No overall differences in safety or effectiveness were observed between patients 65 years of age and older and younger adult patients.

11 DESCRIPTION

DEFENCATH (taurolidine and heparin) CLS contains taurolidine, a thiadiazinane antimicrobial, and heparin sodium, an anti-coagulant.

Taurolidine
Taurolidine is an antimicrobial agent derived from the naturally occurring amino acid taurine. The chemical name is 4,4'-methylenebis(1,2,4-thiadiazinane)-1,1,1',1'-tetraoxide. The molecular weight is 284.36, and the molecular formula is C7H16N4O4S2.

The structural formula of taurolidine is:

Heparin Sodium
Heparin is an anticoagulant consisting of heterogeneous group of straight-chain anionic mucopolysaccharides, called glycosaminoglycans. It is composed of polymers of alternating derivatives of α-D-glucosamido (N-sulfated, O-sulfated, or N-acetylated) and O-sulfated uronic acid (α-L-iduronic acid or β-D-glucuronic acid). Heparin is derived from porcine intestinal mucosa.

The structure of heparin sodium (representative subunits) is:

DEFENCATH is for central venous catheter instillation use. DEFENCATH CLS is available as a sterile, non-pyrogenic, preservative-free, clear, aqueous-based solution of taurolidine and heparin with a pH of 5.5-6.5 in the following strengths:

- 3 mL of catheter lock solution in a single-dose vial containing taurolidine 40.5 mg/3 mL (13.5 mg/mL), and heparin 3,000 USP Units/3 mL (1,000 USP Units/mL)
- 5 mL of catheter lock solution in a single-dose vial containing taurolidine 67.5 mg/5 mL (13.5 mg/mL), and heparin 5,000 USP Units/5 mL (1,000 USP Units/mL)

The heparin potency is determined by a biological assay using a USP reference standard based on units of heparin activity per milligram. The inactive ingredients are 26.1 mg/mL of citric acid, anhydrous (which is added to control pH and maintain the solubility of taurolidine),and may include hydrochloric acid and/or sodium hydroxide for pH adjustment.

12 CLINICAL PHARMACOLOGY

12.1 Mechanism of Action

Heparin
Heparin interacts with the naturally occurring plasma protein, Antithrombin III, to induce a conformational change, which markedly enhances the serine protease activity of Antithrombin III, thereby inhibiting the activated coagulation factors involved in the clotting sequence, particularly Xa and IIa. Small amounts of heparin inhibit Factor Xa, and larger amounts inhibit thrombin (Factor IIa). Heparin also prevents the formation of a stable fibrin clot by inhibiting the activation of the fibrin stabilizing factor. Heparin does not have fibrinolytic activity; therefore, it will not lyse existing clots.

Taurolidine
Taurolidine is an antimicrobial drug [see Microbiology (12.4)].

12.2 Pharmacodynamics

The pharmacodynamics of DEFENCATH are unknown.

12.3 Pharmacokinetics

No pharmacokinetic studies were conducted because DEFENCATH is intended to be instilled into the catheter lumens at the conclusion of each HD session for patients with kidney failure requiring chronic HD. DEFENCATH is not intended for systemic administration [see Dosage and Administration (2)].

12.4 Microbiology

Mechanism of Action
The mechanism of action of taurolidine and its metabolites is non-specific, causing damage to microbial cell walls and inhibiting adherence of microorganisms to biological surfaces.

Resistance
Time kill studies showed that taurolidine is bactericidal (>3 log10 CFU reduction) at 1x to 4x minimum inhibitory concentration (MIC). The frequency of resistant mutants was <10^-9 at 2x and 4x MIC for two strains each of Escherichia coli, Staphylococcus aureus, Enterococcus faecalis, Enterococcus faecium and Pseudomonas aeruginosa.^1

Antimicrobial Activity
The following in vitro data are available but their clinical significance is unknown. Taurolidine has been shown to be active against most isolates of the following microorganisms:

Gram-positive
Staphylococcus aureus (including methicillin-sensitive Staphylococcus aureus (MSSA) and methicillin-resistant Staphylococcus aureus (MRSA))
Staphylococcus epidermidis
Enterococcus faecalis

Gram-negative
Escherichia coli
Klebsiella pneumoniae
Pseudomonas aeruginosa
Serratia marcescens

Fungi
Candida albicans
Candida glabrata

13 NONCLINICAL TOXICOLOGY

13.1 Carcinogenesis, Mutagenesis, Impairment of Fertility

Carcinogenesis
Carcinogenicity studies in animals have not been conducted with taurolidine or heparin.

Mutagenesis
Taurolidine was positive in vitro in an Ames reverse mutation assay and it increased mutation frequency in L5178Y mouse lymphoma cells. However, taurolidine was negative in an in vivo combined micronucleus test and comet assay in rats at the highest dose tested, 600 mg/kg/day administered intravenously.

No studies have been conducted with heparin to determine its mutagenic potential.

Impairment of Fertility
Fertility studies have not been conducted with DEFENCATH due to its negligible clinical exposure.

14 CLINICAL STUDIES

The efficacy and safety of DEFENCATH for reducing the incidence of CRBSI in patients with kidney failure receiving chronic HD was evaluated in LOCK-IT-100 (referred to as Trial 1, NCT02651428), a randomized, double-blind, active-controlled, multicenter trial.

A total of 806 patients were randomized in a 1:1 ratio to receive either DEFENCATH or heparin (heparin sodium USP 1,000 units/mL, benzyl alcohol 9.45 mg/mL and sodium chloride 9.0 mg/mL) as a CLS. Enrollment in Trial 1 was not limited to patients with specific types of HD catheters. DEFENCATH or heparin was instilled into central venous HD catheters at the end of all dialysis sessions and was withdrawn prior to the initiation of the next dialysis session. The median age of the study population was 63 years (range 21-94 years); 58% identified as males and 63% identified as white. The majority of patients (98%) had HD treatment three times per week, and 48% had their catheter implanted within three months prior to randomization.

A clinical adjudication committee (CAC) assessed the cases of CRBSI. The CAC definition for CRBSI included one positive blood culture (other than for coagulase-negative staphylococci, which required a confirmatory culture) from a peripheral site or either the arterial or venous catheter hub or the arterial or venous dialysis blood line and the patient had to have signs and symptoms of infection and no other apparent source of bloodstream infection.

Results of analyses of CAC-adjudicated CRBSI among the DEFENCATH and heparin groups in all randomized patients who received at least one dose of allocated study CLS are presented in Table 3. Patients in the DEFENCATH group had a lower incidence of CRBSI events compared to patients in the control group.

Table 3. Results of Analyses of CAC-Adjudicated CRBSI in Patients with Kidney Failure Receiving HD in Trial 1
 | DEFENCATH (N=397) | Heparin (N=398)
CAC-adjudicated CRBSI | 9 (2.3%) | 32 (8.0%)
Event rate per 1000 catheter-days (95% CI) | 0.13 (0.07, 0.26) | 0.46 (0.33, 0.66)
Risk reduction (95% CI) [Based on 1 – Hazard Ratio] | 71% (38%, 86%)
Log-rank test p-value | 0.0006

In total, 5% [18/397] of subjects in the DEFENCATH arm and 5% [21/398] of subjects in the heparin arm died during the trial (difference [DEFENCATH – Heparin]: -0.7% with a 95% CI[-3.7%, 2.3%]).

Among the 9 patients in the DEFENCATH arm with a CAC-adjudicated CRBSI, 1 had a gram-negative organism isolated and 8 had a gram-positive organism isolated; among the 32 patients in the heparin arm with a CAC-adjudicated CRBSI, 14 had a gram-negative organism isolated and 18 had a gram-positive organism isolated.

15 REFERENCES

1. Torres-Viera, C, Thauvin-Eliopoulos C., Souli M, DeGirolamin P, Farris MG Wennerstein CB, Sofia RD and Eliopoulos GM. 2000.Antimicrobial Agents and Chemotherapy 44(6): 1720 - 1724.

16 HOW SUPPLIED/STORAGE AND HANDLING

DEFENCATH cathether lock solution is available in:

- 3 mL of catheter lock solution in a single-dose vial containing taurolidine 40.5 mg/3 mL (13.5 mg/mL), and heparin 3,000 USP Units/3 mL (1,000 USP Units/mL) (NDC 72990-103-03)
- 5 mL of catheter lock solution in a single-dose vial containing taurolidine 67.5 mg/5 mL (13.5 mg/mL), and heparin 5,000 USP Units/5 mL (1,000 USP Units/mL) (NDC 72990-105-05)

Each vial contains a sterile, preservative-free, clear aqueous-based solution for instillation in central venous catheters. Each carton contains 10 single-dose vials.

DEFENCATH vials must be stored at a controlled room temperature of 20°C to 25°C (68°F to 77°F); excursions are permitted from 15°C to 30°C (59°F to 86°F) [see USP Controlled Room Temperature]. Do not freeze. DEFENCATH vials must be stored in the commercial carton, prior to the instillation in central venous catheters.

Manufactured for:
CorMedix Inc.
300 Connell Drive, Suite 4200
Berkeley Heights, NJ 07922

PRINCIPAL DISPLAY PANEL

NDC 72990-103-10

Rx Only

DEFENCATH®

Taurolidine and Heparin Catheter Lock Solution

Limited
Population*

Taurolidine 40.5 mg/3 mL (13.5 mg/mL) and
Heparin 3,000 USP Units/3 mL (1,000 USP Units/mL)

Derived from Porcine Intestinal Mucosa

3 mL

For Instillation in Central Venous Catheters
Not for systemic administration. Do not use as a catheter lock flush

*See prescribing information for DEFENCATH for
information about the limited population.

Contains 10 Single-dose vials.
Discard unused portion.

CorMedix Inc.®

PRINCIPAL DISPLAY PANEL

NDC 72990-103-03

Rx Only

DEFENCATH®

Taurolidine and Heparin Catheter Lock Solution

Limited
Population*

Taurolidine 40.5 mg/3 mL (13.5 mg/mL)
and Heparin 3,000 USP Units/3 mL
(1,000 USP Units/mL)

Derived from Porcine Intestinal Mucosa

For Instillation in Central Venous
Catheters
Not for systemic administration
Do not use as a catheter lock flush

Store at 20°C to 25°C
(68°F to 77°F)

3 mL Fill Single-Dose Vial
Discard Unused Portion

PRINCIPAL DISPLAY PANEL

NDC 72990-105-10

Rx Only

DEFENCATHTM

Taurolidine and Heparin Catheter Lock Solution

Limited
Population*

Taurolidine 67.5 mg/5mL (13.5 mg/mL) and
Heparin 5,000 USP Units/5 mL (1,000 USP Units/mL)

Derived from Porcine Intestinal Mucosa

5 mL

For Instillation in Central Venous Catheters
Not for systemic administration
Do not use as a catheter lock flush

*See prescribing information for
Defencath for information about
the limited population.

Contains 10 Single-dose vials.
Discard unused portion.

CorMedix Inc.TM

PRINCIPAL DISPLAY PANEL

NDC 72990-105-05

Rx Only

DEFENCATHTM

Taurolidine and Heparin Catheter Lock Solution

Limited
Population*

Taurolidine 67.5 mg/5mL (13.5 mg/mL)
and Heparin 5,000 USP Units/5 mL
(1,000 USP Units/mL)

Derived from Porcine Intestinal Mucosa

For Instillation in Central Venous
Catheters
Not for systemic administration
Do not use as a catheter lock flush

Store at 20°C to 25°C
(68°F to 77°F)

5 mL Fill Single-Dose Vial -
Discard Unused Portion